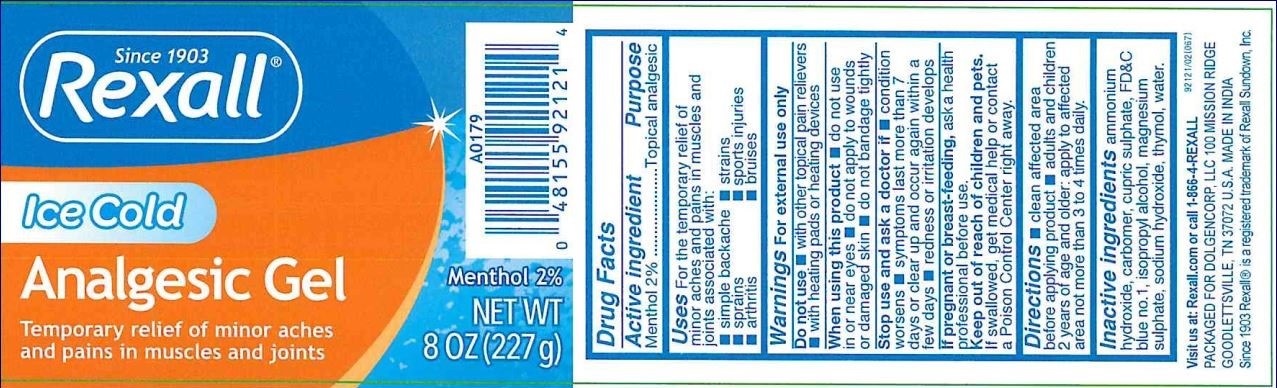 DRUG LABEL: Rexall ICE COLD ANALGESIC
NDC: 55910-088 | Form: GEL
Manufacturer: Dolgencorp, LLC
Category: otc | Type: HUMAN OTC DRUG LABEL
Date: 20181004

ACTIVE INGREDIENTS: MENTHOL 2 g/100 g
INACTIVE INGREDIENTS: CARBOXYPOLYMETHYLENE; CUPRIC SULFATE; MAGNESIUM SULFATE, UNSPECIFIED; THYMOL; FD&C BLUE NO. 1; ISOPROPYL ALCOHOL; SODIUM HYDROXIDE; WATER

Active ingredient

Menthol 2%

Purpose

Topical Analgesic

Uses

For the temporary relief of monor aches and pains in muscles and joints associated with:

■ simple backache
■ sprains

■ arthritis

■ strains

■ sports injuries

■ bruises

Warnings

For external use only

Do not use

■ with other topical pain relievers

■ with heating pads or heating devices

When using this product

■ do not use in or near eyes ■ do not apply to wounds or damaged skin ■ do not bandage tightly

Stop use and ask a doctor if

■ condition worsens ■ symptoms last for more than 7 days or clear up and occur again within a few days ■ redness or irritation develops

If pregnant or breast-feeding

ask a health professional before use

Keep out of reach of children and pets. If swallowed, get medical help or contact a Poison Control Center right away.

Directions

■ clean affected area before applying product ■ adults and children 2 years of age and older: apply to affected area not more than 3 to 4 times daily

Inactive Ingredients

ammonium hydroxide, carbomer, cupric sulphate, FD&C blue no. 1, isopropyl alcohol, magnesium sulphate, sodium hydroxide, thymol, water